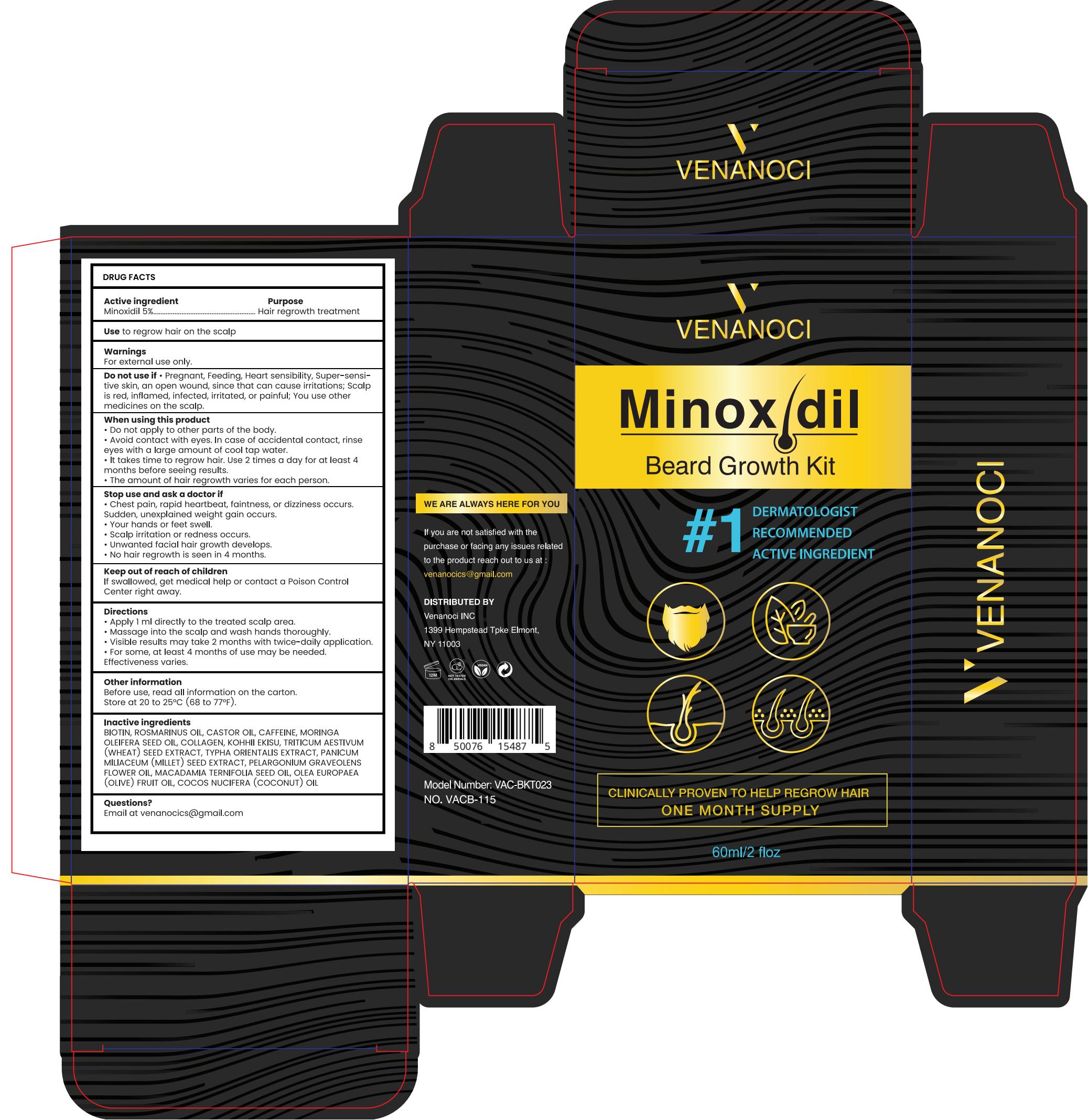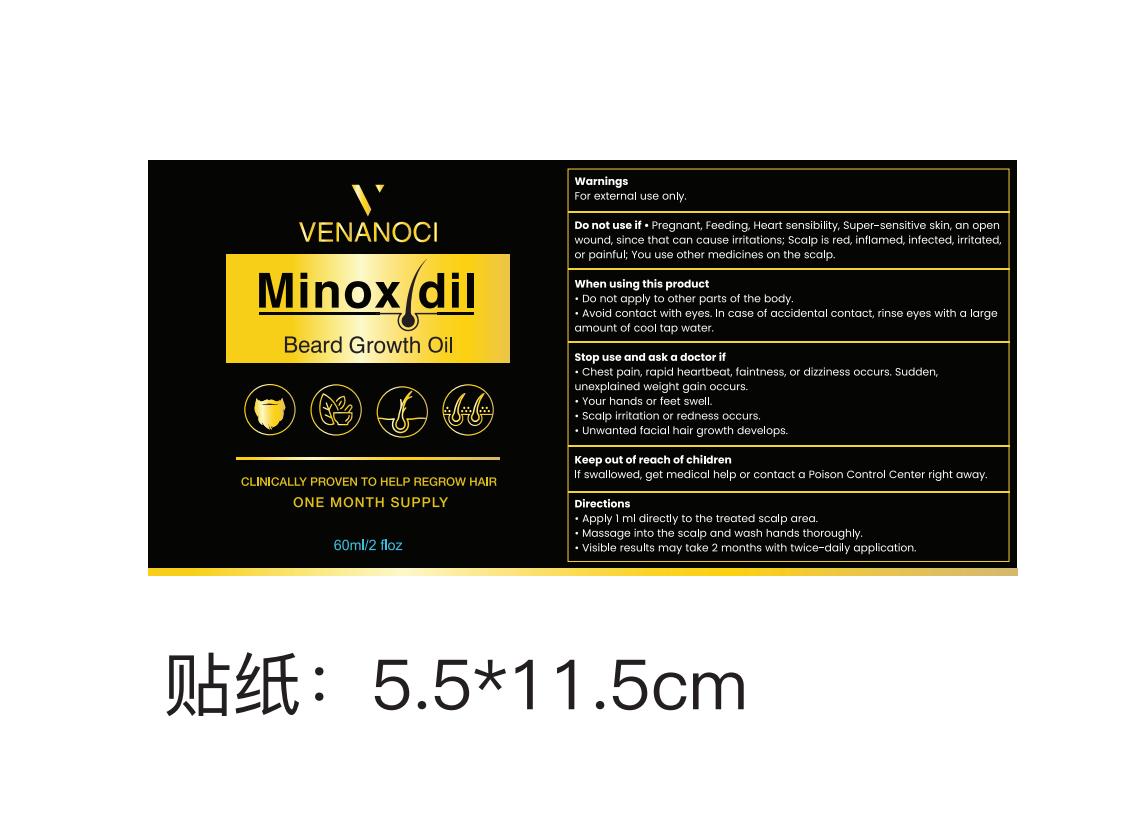 DRUG LABEL: VENANOCI Minoxidil
NDC: 83818-029 | Form: SOLUTION
Manufacturer: Shenzhen Xinxin Yunhai Technology Co., Ltd.
Category: otc | Type: HUMAN OTC DRUG LABEL
Date: 20260214

ACTIVE INGREDIENTS: MINOXIDIL 5 g/100 mL
INACTIVE INGREDIENTS: MACADAMIA TERNIFOLIA SEED OIL; MILLET; OLEA EUROPAEA (OLIVE) FRUIT OIL; COCOS NUCIFERA (COCONUT) OIL; MORINGA OLEIFERA SEED OIL; TYPHA ORIENTALIS WHOLE; ROSEMARY OIL; CASTOR OIL; CAFFEINE; COLLAGEN, SOLUBLE, FISH SKIN; PELARGONIUM GRAVEOLENS FLOWER OIL; BIOTIN; WHEAT

83818-029

Active Ingredient

Minoxidil 5%

Purpose

Hair regrowth treatment

Use

to regrow hair on the scalp

Warnings

For external use only.

Do not use

Pregnant, Feeding, Heart sensibility, Super-sensitive skin, an open wound, since that can cause irritations; Scalp is red, inflamed, infected, irritated, or painful; You use other medicines on the scalp.

When Using

• Do not apply to other parts of the body.
• Avoid contact with eyes. In case of accidental contact, rinse eyes with a large amount of cool tap water.
• It takes time to regrow hair. Use 2 times a day for at least 4 months before seeing results.
• The amount of hair regrowth varies for each person.

Stop Use

• Chest pain, rapid heartbeat, faintness, or dizziness occurs. Sudden, unexplained weight gain occurs.
• Your hands or feet swell.
• Scalp irritation or redness occurs.
• Unwanted facial hair growth develops.
• No hair regrowth is seen in 4 months.

Ask Doctor

• Chest pain, rapid heartbeat, faintness, or dizziness occurs. Sudden, unexplained weight gain occurs.
• Your hands or feet swell.
• Scalp irritation or redness occurs.
• Unwanted facial hair growth develops.
• No hair regrowth is seen in 4 months.

Keep Out Of Reach Of Children

If swallowed, get medical help or contact a Poison Control Center right away.

Directions

• Apply 1ml directly to the treated scalp area.
• Massage into the scalp and wash hands thoroughly.
• Visible results may take 2 months with twice-daily application.
• For some, at least 4 months of use may be needed. Effectiveness varies.

Other information

Before use, read all information on the carton.
Store at 20 to 25°C (68 to 77°F).

Inactive ingredients

BIOTIN, ROSMARINUS OIL, CASTOR OIL, CAFFEINE, MORINGA OLEIFERA SEED OIL, COLLAGEN, KOHHII EKISU, TRITICUM AESTIVUM (WHEAT) SEED EXTRACT, TYPHA ORIENTALIS EXTRACT, PANICUM MILIACEUM (MILLET) SEED EXTRACT, PELARGONIUM GRAVEOLENS FLOWER OIL, MACADAMIA TERNIFOLIA SEED OIL, OLEA EUROPAEA (OLIVE) FRUIT OIL, COCOS NUCIFERA (COCONUT) OIL

Questions

Email at venanocics@gmail.com